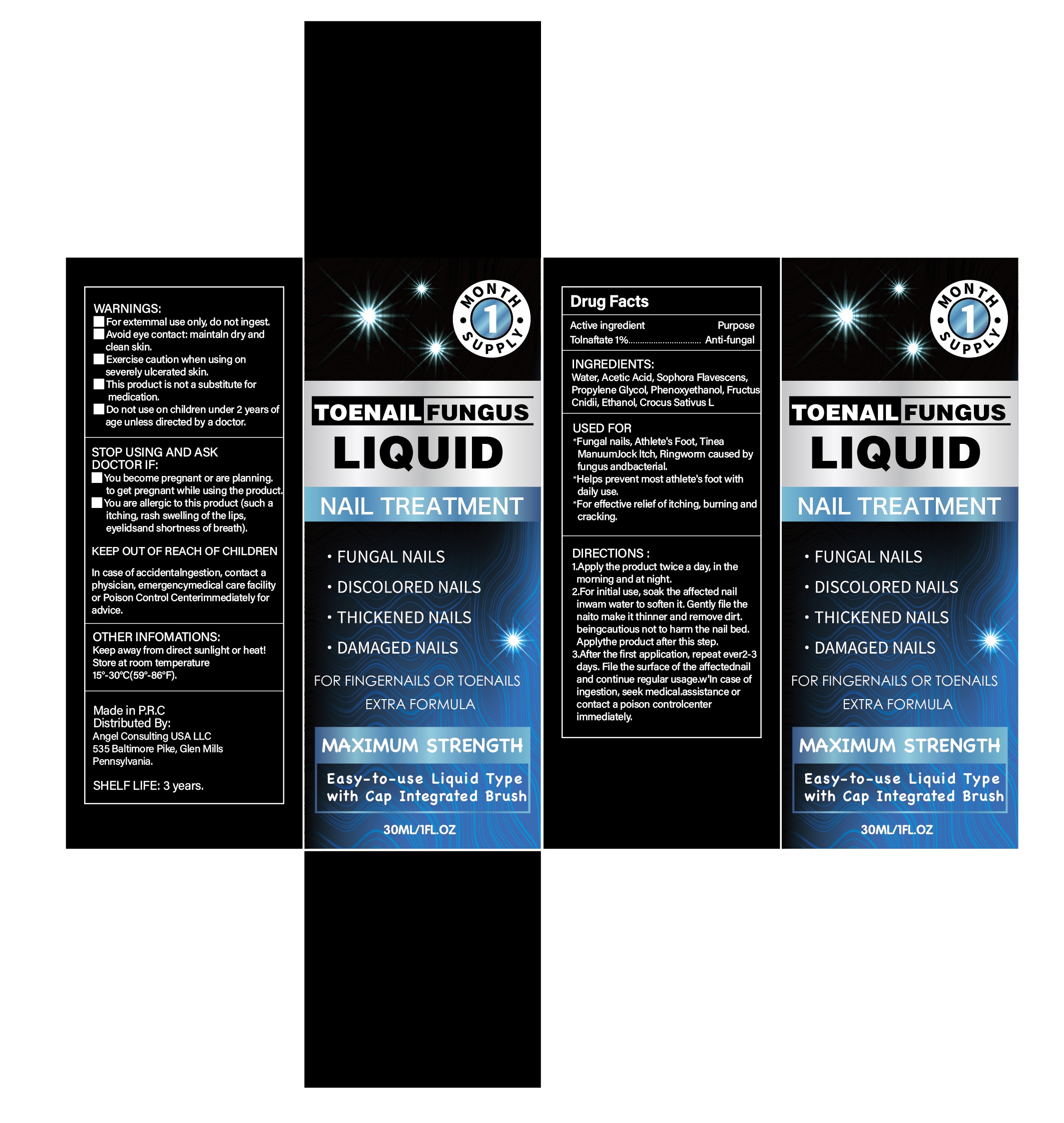 DRUG LABEL: Anti-Fungal Liquid
NDC: 84033-003 | Form: LIQUID
Manufacturer: Qingdao Kuajie Online Electronic Technology Co., Ltd
Category: otc | Type: HUMAN OTC DRUG LABEL
Date: 20240401

ACTIVE INGREDIENTS: TOLNAFTATE 1 g/100 mL
INACTIVE INGREDIENTS: ALCOHOL 10 mL/100 mL; ANGELICA DAHURICA LEAF 1.8 g/100 mL; SORBITOL 15 g/100 mL; SALICYLIC ACID 4.7 g/100 mL; LAUROCAPRAM 0.3 g/100 mL; PROPANEDIOL 6 g/100 mL; CHLORHEXIDINE 0.2 g/100 mL; POLIGLUSAM 3.4 g/100 mL; WATER 58.6 mL/100 mL

ACTIVE INGREDIENT

Tolnaftate 1%

INACTIVE INGREDIENT

WATER 58.6 mL
POLIGLUSAM 3.4 g
CHLORHEXIDINE 0.2 g
PROPANEDIOL 6 g
LAUROCAPRAM 0.3 g
SALICYLIC ACID 4.7 g
SORBITOL 15 g
ANGELICA DAHURICA LEAF 1.8 g
ALCOHOL 10 mL

PURPOSE

Fungal Nail Renewal

HOW TO USE

1.Apply the product twice a day, in themorning and at night.

2.For initial use, soak the affected nail inwam water to soften it. Gently file the naito make it thinner and remove dirt. beingcautious not to harm the nail bed. Applythe product after this step.

3.After the first application, repeat ever2-3 days. File the surface of the affectednail and continue regular usage.w'In case of ingestion, seek medical.assistance or contact a poison controlcenter immediately.

WARNINGS

For extemmal use only, do not ingest.

Avoid eye contact: maintaln dry and clean skin.

Exercise caution when using on severely ulcerated skin.

This product is not a substitute for medication.

Do not use on children under 2 years of age unless directed by a doctor.

STOP USE AND ASK A DOCTOR IF

You become pregnant or are planning.to get pregnant while using the product.

You are allergic to this product (such a itching, rash swelling of the lips, eyelidsand shortness of breath).

WHEN USING THIS PRODUCT

Fungal nails, Athlete's Foot, Tinea ManuumJock ltch, Ringworm caused by fungus andbacterial.

Helps prevent most athlete's foot with daily use.

For effective relief of itching, burning and cracking.

STORAGE

Store at room temperature

15°-30℃(59°-86℉).

KEEP OUT OF REACH OF CHILDREN

Keep away from direct sunlight or heat!

DOSAGE

1.Apply the product twice a day, in themorning and at night.

2.For initial use, soak the affected nail inwam water to soften it. Gently file the naito make it thinner and remove dirt. beingcautious not to harm the nail bed. Applythe product after this step.

3.After the first application, repeat ever2-3 days. File the surface of the affectednail and continue regular usage.w'In case of ingestion, seek medical.assistance or contact a poison controlcenter immediately.